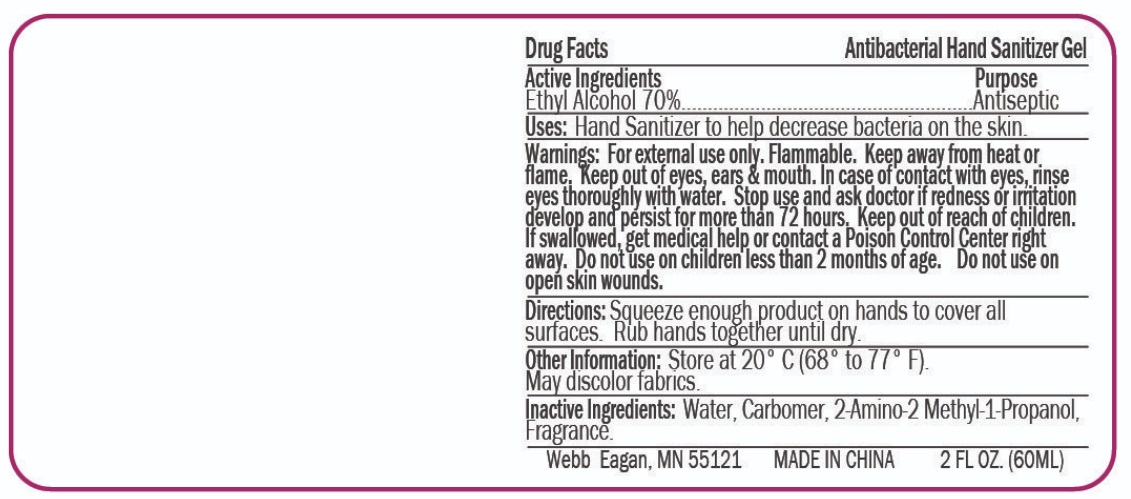 DRUG LABEL: Antibacterial Hand Sanitizer
NDC: 70445-060 | Form: GEL
Manufacturer: Webb Business Promotions, Incorporated
Category: otc | Type: HUMAN OTC DRUG LABEL
Date: 20200922

ACTIVE INGREDIENTS: ALCOHOL 70 mL/100 mL
INACTIVE INGREDIENTS: CARBOMER 980; AMINOMETHYLPROPANOL; WATER

70445-060-01 dongyang medical 60ml gel

Active Ingredient(s)

Alcohol 70% v/v. Purpose: Antiseptic

Purpose

Antiseptic, Hand Sanitizer

Use

Hand Sanitizer to help decrease bacteria on the skin.

Warnings

For external use only. Flammable. Keep away from heat or flame. Keep out of eyes, ears & mouth. In case of contact with eyes, rinse eyes thoroughly with water. Stop use and ask doctor if redness or irritation develop and persist for more than 72 hours. Keep out of reach of children. If swallowed, get medical help or contact a Poison Control Center right away. Do not use on childeren less than 2 months of age. Do not use on open skin wounds.

When using this product keep out of eyes, ears, and mouth. In case of contact with eyes, rinse eyes thoroughly with water.
Stop use and ask a doctor if irritation or rash occurs. These may be signs of a serious condition.
Keep out of reach of children. If swallowed, get medical help or contact a Poison Control Center right away.

Stop use and ask doctor if redness or irritation develop and persist for more than 72 hours.

Directions

Squeeze enough product on hands to cover all surface. Rub hands together until dry.

Other information

- Store at 20℃ (68-77℉)
- May discolor fabrics.

Inactive ingredients

Water, Carbomer, 2-Amino-2-Methyl-1-Propanol, Fragrance.

Package Label - Principal Display Panel

60 mL NDC: 70445-060-01